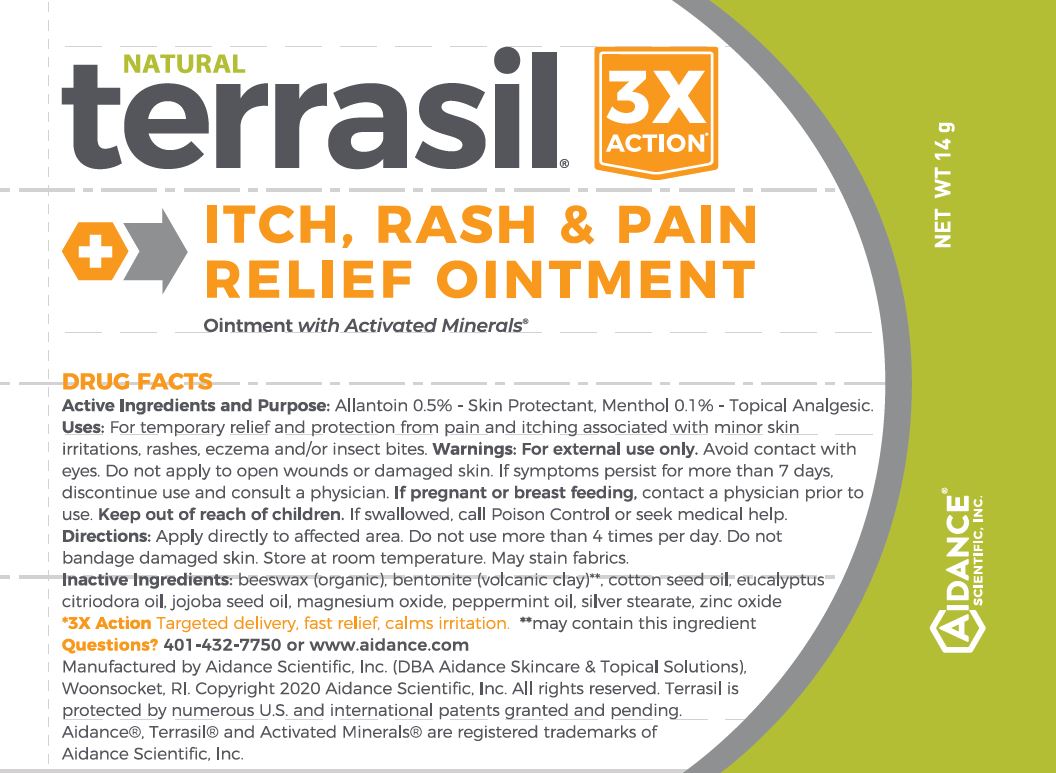 DRUG LABEL: Terrasil Itch, Rash and Pain Relief
NDC: 24909-159 | Form: OINTMENT
Manufacturer: Aidance Skincare & Topical Solutions, LLC
Category: otc | Type: HUMAN OTC DRUG LABEL
Date: 20250711

ACTIVE INGREDIENTS: ALLANTOIN 0.5 g/100 g; MENTHOL 0.1 g/100 g
INACTIVE INGREDIENTS: BENTONITE; COTTONSEED OIL; EUCALYPTUS OIL; JOJOBA OIL; MAGNESIUM OXIDE; PEPPERMINT OIL; SILVER OXIDE; STEARIC ACID; WHITE WAX; ZINC OXIDE

24909-159 terrasil Itch, Rash and Pain Relief

Active Ingredients

Allantoin 0.5%, Menthol 0.1%

Purpose

Allantoin - Skin Protectant
Menthol - Topical Anesthetic

Uses

For temporary relief and protection from pain and itching associated with minor skin irritations, rashes, eczema and/or insect bites.

Warnings

For external use only. Avoid contact with eyes. Do not apply to open wounds or damaged skin. If symptoms persist for more than 7 days, discontinue use and consult physician. If pregnant or breast feeding, contact physician prior to use.

Keep out of reach of children. If swallowed, call Poison Control or seek medical help.

Directions

Apply directly to affected area. Do not use more than 4 times per day. Do not bandage damaged skin. Store at room temperature. May temporarily (washable) discolor skin and fabrics in sunlight.

Inactive Ingredients

beeswax, cottonseed oil, eucalyptus oil, jojoba oil, magnesium oxide, peppermint oil, silver stearate, zinc oxide.